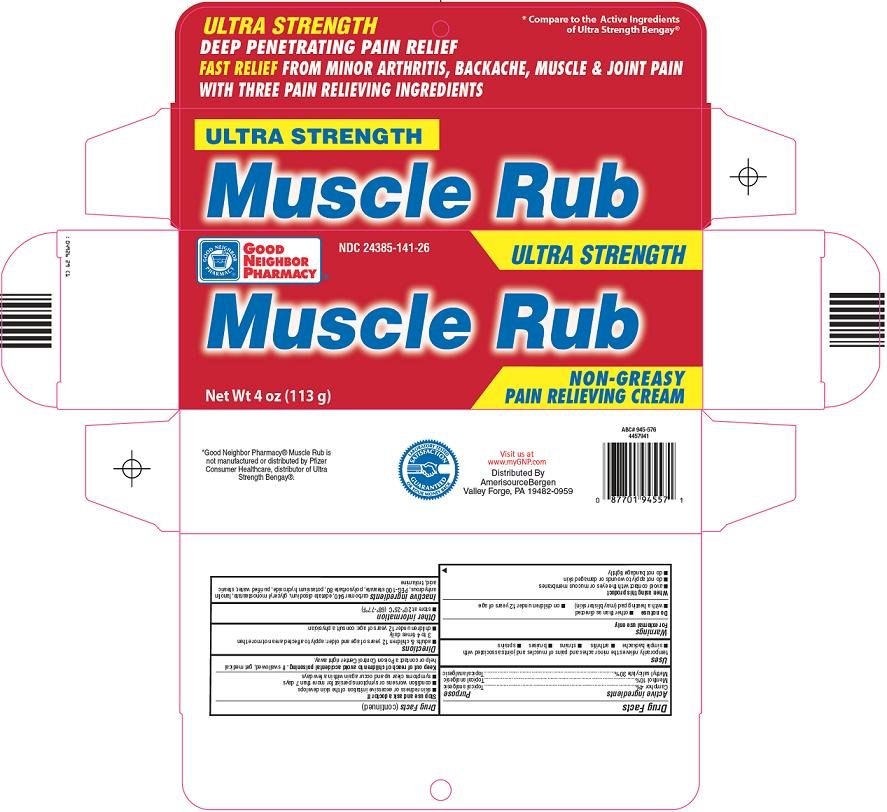 DRUG LABEL: Good Neighbor Pharmacy Muscle Rub
NDC: 24385-141 | Form: CREAM
Manufacturer: Amerisource Bergen
Category: otc | Type: HUMAN OTC DRUG LABEL
Date: 20090527

ACTIVE INGREDIENTS: CAMPHOR (SYNTHETIC) 4 g/100 g; MENTHOL 10 g/100 g; METHYL SALICYLATE 30 g/100 g
INACTIVE INGREDIENTS: CARBOMER HOMOPOLYMER TYPE C; EDETATE DISODIUM; GLYCERYL MONOSTEARATE; POLYOXYL 100 STEARATE; POLYSORBATE 80; POTASSIUM HYDROXIDE; WATER; STEARIC ACID; TROLAMINE

Amerisource Bergen Muscle Rub Drug Facts

Active ingredient

Camphor 4%

Menthol 10%

Methyl salicylate 30%

Purpose

Topical analgesic

Uses

temporarily relieves the minor aches and pains of muscles and joints associated with

- simple backache
- arthritis
- strains
- bruises
- sprains

Warnings

For external use only

Do not use

- other than as directed
- with a heating pad (may blister skin)
- on children under 12 years of age

When using this product

- avoid contact with the eyes or mucous membranes
- do not apply to wounds or damaged skin
- do not bandage tightly

Stop use and ask a doctor if

- skin redness or excessive irritation of the skin develops
- condition worsens or symptoms persist for more than 7 days
- symptoms clear up and occur again within a few days

Keep out of reach of children to avoid accidental poisoning.

If swallowed, get medical help or contact a Poison Control Center right away.

Directions

- adults & children 12 years of age and older: apply to affected area not more than 3 to 4 times daily
- children under 12 years of age: consult a physician

Other information

- store at 20°-25°C (68°-77°F)

Inactive ingredients

carbomer 940, edetate disodium, glyceryl monostearate, lanolin anhydrous, PEG-100 stearate, polysorbate 80, potassium hydroxide, purified water, stearic acid, trolamine

Principal Display Panel

Compare to the Active Ingredients of Ultra Strength Bengay®

Ultra Strength

Deep Penetrating Pain Relief

Fast Relief from Minor Arthritis, Backache, Muscle & Joint Pain

With Three Pain Relieving Ingredients

Muscle Rub

Non-Greasy

Pain Relieving Cream

Muscle Rub Carton